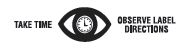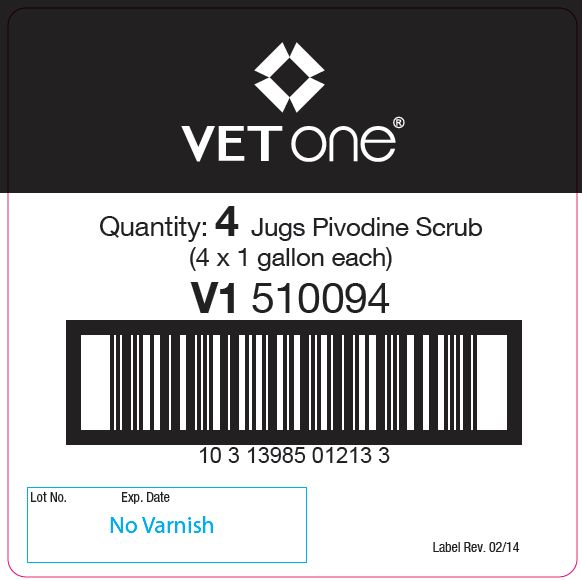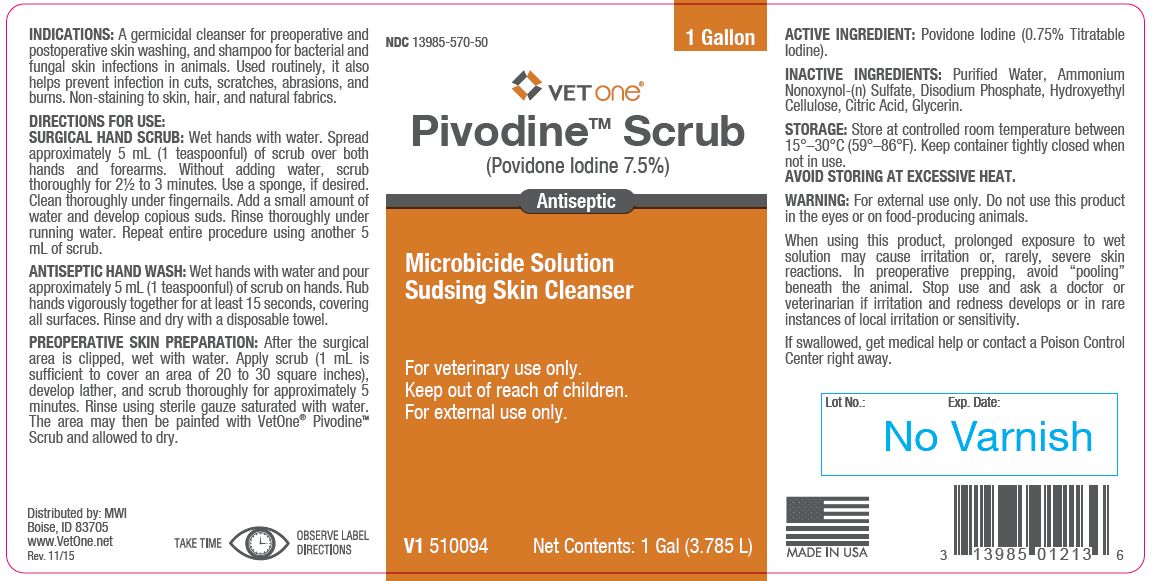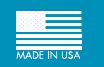 DRUG LABEL: Pivodine
NDC: 13985-570 | Form: SOLUTION
Manufacturer: MWI/Vet One
Category: animal | Type: OTC ANIMAL DRUG LABEL
Date: 20241115

ACTIVE INGREDIENTS: POVIDONE-IODINE 5.1 g/1 L

PivodineTM Scrub
(Povidone Iodine 7.5%)
Antiseptic

PURPOSE

Microbicide Solution Sudsing Skin Cleanser

KEEP OUT OF REACH OF CHILDREN

For veterinary use only.
Keep out of reach of children.
For external use only.

INDICATIONS:

A germicidal cleanser for preoperative and postoperative skin washing, and shampoo for bacterial and fungal skin infections in animals. Used routinely, it also helps prevent infection in cuts, scratches, abrasions, and burns. Non-staining to skin, hair, and natural fabrics.

DIRECTIONS FOR USE:

SURGICAL HAND SCRUB: Wet hands with water. Spread approximately 5 mL (1 teaspoonful) of scrub over both hands and forearms. Without adding water, scrub thoroughly for 2½ to 3 minutes. Use a sponge, if desired. Clean thoroughly under fingernails. Add a small amount of water and develop copious suds. Rinse thoroughly under running water. Repeat entire procedure using another 5 mL of scrub.

DOSAGE AND ADMINISTRATION

ANTISEPTIC HAND WASH: Wet hands with water and pour approximately 5 mL (1 teaspoonful) of scrub on hands. Rub hands vigorously together for at least 15 seconds, covering all surfaces. Rinse and dry with a disposable towel.

DOSAGE AND ADMINISTRATION

PREOPERATIVE SKIN PREPARATION: After the surgical area is clipped, wet with water. Apply scrub (1 mL is sufficient to cover an area of 20 to 30 square inches), develop lather, and scrub thoroughly for approximately 5 minutes. Rinse using sterile gauze saturated with water. The area may then be painted with VetOne® PivodineTM Scrub and allowed to dry.

ACTIVE INGREDIENT:

Povidone Iodine (0.75% Titratable Iodine).

INACTIVE INGREDIENTS:

Purified Water, Ammonium Nonoxynol-(n) Sulfate, Disodium Phosphate, Hydroxyethyl Cellulose, Citric Acid, Glycerin.

STORAGE:

Store at controlled room temperature between 15°–30°C (59°–86°F). Keep container tightly closed when not in use.

AVOID STORING AT EXCESSIVE HEAT.

Net Contents:

1 Gal (3.785 L) V1 510094

INFORMATION FOR OWNERS/CAREGIVERS

Distributed by: MWI
Boise, ID 83705
www.VetOne.net
Rev. 11/15